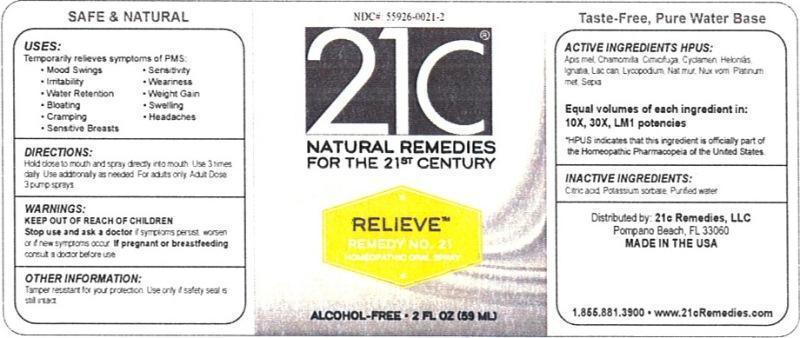 DRUG LABEL: Relieve Remedy No. 21
NDC: 55926-0021 | Form: LIQUID
Manufacturer: Speer Laboratories, LLC
Category: homeopathic | Type: HUMAN OTC DRUG LABEL
Date: 20130730

ACTIVE INGREDIENTS: APIS MELLIFERA 10 [hp_X]/59 mL; MATRICARIA RECUTITA 10 [hp_X]/59 mL; BLACK COHOSH 10 [hp_X]/59 mL; CYCLAMEN PURPURASCENS TUBER 10 [hp_X]/59 mL; CHAMAELIRIUM LUTEUM ROOT 10 [hp_X]/59 mL; STRYCHNOS IGNATII SEED 10 [hp_X]/59 mL; CANIS LUPUS FAMILIARIS MILK 10 [hp_X]/59 mL; LYCOPODIUM CLAVATUM SPORE 10 [hp_X]/59 mL; SODIUM CHLORIDE 10 [hp_X]/59 mL; STRYCHNOS NUX-VOMICA SEED 10 [hp_X]/59 mL; PLATINUM 10 [hp_X]/59 mL; SEPIA OFFICINALIS JUICE 10 [hp_X]/59 mL
INACTIVE INGREDIENTS: WATER; CITRIC ACID MONOHYDRATE; POTASSIUM SORBATE

Relieve Remedy No. 21

ACTIVE INGREDIENT

Active Ingredients HPUS: Apis mellifica, Chamomilla, Cimicifuga racemosa, Cyclamen europaeum, Helonias dioica, Ignatia amara, Lac caninum, Lycopodium clavatum, Natrum muriaticum, Nux vomica, Platinum metallicum, Sepia.

Equal volumes of each ingredient in: 10X, 30X, LM1 potencies

HPUS indicates that this ingredient is officially part of the Homeopathic Pharmacopeia of the United States.

Inactive Ingredients: Citric acid, Potassium sorbate, Purified water.

INDICATIONS AND USAGE

Uses: Temporarily relieves symptoms of PMS:

- mood swings
- irritability
- water retention
- bloating
- cramping
- sensitive breasts
- sensitivity
- weariness
- weight gain
- swelling
- headaches

Directions:

Hold close to mouth and spray directly into mouth. Use 3 times daily. Use additionally as needed. For adults only. Adult dose: 3 pump sprays.

Keep out of reach of children.

WARNINGS

Warnings: Stop use and ask a doctor if symptoms persist, worsen or if new symptoms occur. If pregnant or breastfeeding, consult a doctor before use.

OTHER SAFETY INFORMATION

Tamper resistant for your protection. Use only if safety seal is still intact.

PURPOSE

Uses: Temporarily relieves symptoms of PMS: mood swings, irritability, water retention, bloating, cramping, sensitive breasts, sensitivity, weariness, weight gain, swelling, headaches